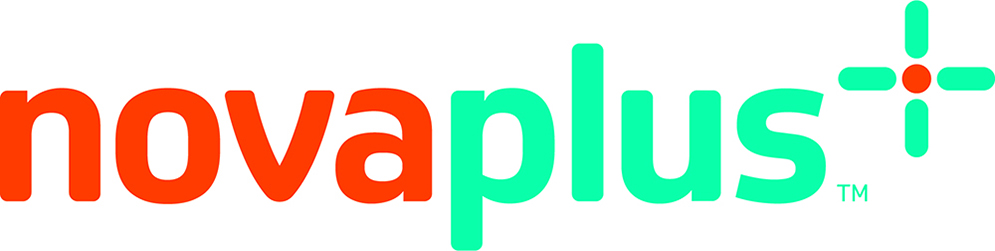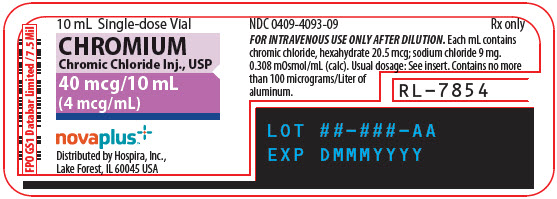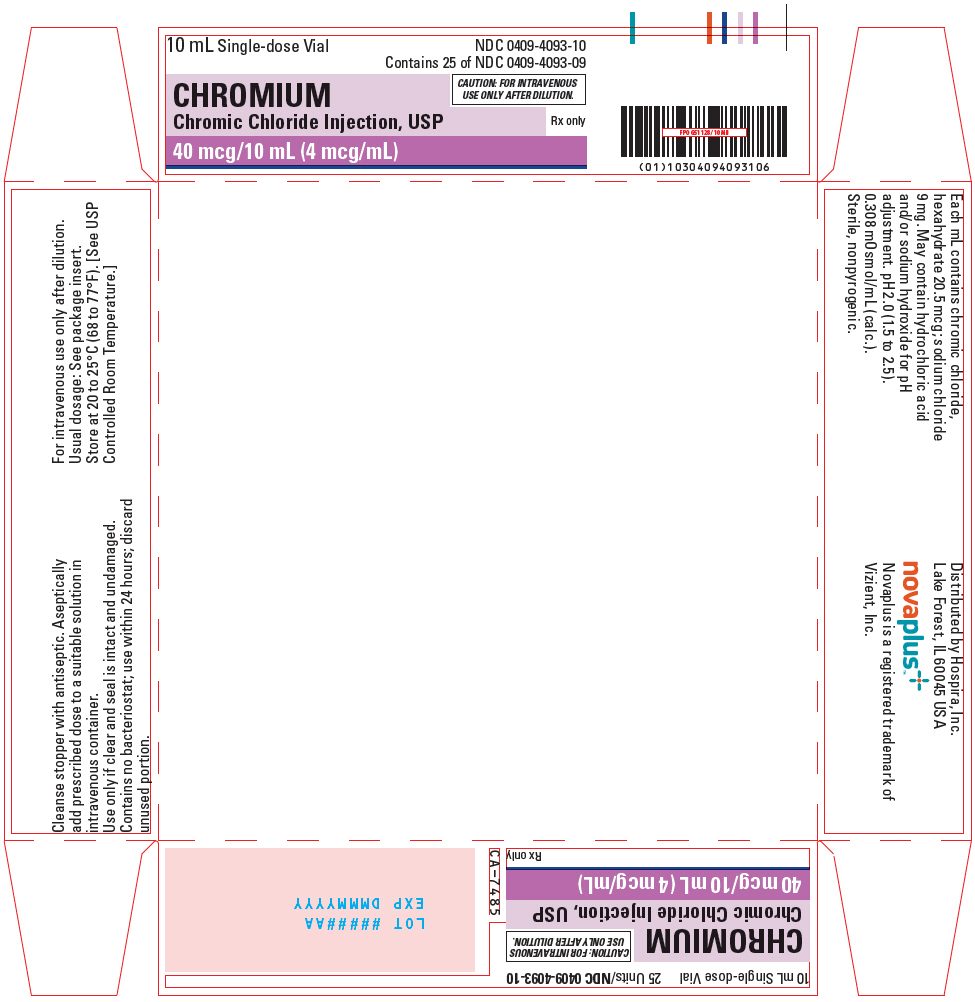 DRUG LABEL: Chromium
NDC: 0409-4093 | Form: INJECTION, SOLUTION
Manufacturer: Hospira, Inc.
Category: prescription | Type: HUMAN PRESCRIPTION DRUG LABEL
Date: 20241129

ACTIVE INGREDIENTS: CHROMIC CHLORIDE 4 ug/1 mL
INACTIVE INGREDIENTS: SODIUM CHLORIDE 9 mg/1 mL; HYDROCHLORIC ACID; SODIUM HYDROXIDE

CHROMIUM
Chromic Chloride
Injection, USP
40 mcg/10 mL (4 mcg/mL)

FOR I.V. USE ONLY AFTER DILUTION
Plastic Vial

Rx only

DESCRIPTION

Chromium 4 mcg/mL (Chromic Chloride Injection, USP) is a sterile, nonpyrogenic solution intended for use as an additive to intravenous solutions for total parenteral nutrition (TPN). Each mL of solution contains 20.5 mcg chromic chloride, hexahydrate and 9 mg sodium chloride. The solution contains no bacteriostat, antimicrobial agent, or added buffer. The pH is 2.0 (1.5 to 2.5); product may contain hydrochloric acid and/or sodium hydroxide for pH adjustment. The osmolarity is 0.308 mOsm/mL (calc.).

Chromic Chloride, USP is chemically designated chromic chloride, hexahydrate CrCl3 • 6H2O, a crystalline compound soluble in water.

Sodium Chloride, USP is chemically designated NaCl, a white, crystalline compound freely soluble in water.

The semi-rigid vial is fabricated from a specially formulated polyolefin. It is a copolymer of ethylene and propylene. The safety of the plastic has been confirmed by tests in animals according to USP biological standards for plastic containers. The small amount of water vapor that can pass through the plastic container wall will not significantly alter the drug concentration.

CLINICAL PHARMACOLOGY

Trivalent chromium is part of glucose tolerance factor, an essential activator of insulin-mediated reactions. Chromium helps to maintain normal glucose metabolism and peripheral nerve function.

Providing chromium during TPN helps prevent deficiency symptoms including impaired glucose tolerance, ataxia, peripheral neuropathy and a confusional state similar to mild/moderate hepatic encephalopathy.

Serum chromium is bound to transferrin (siderophilin) in the beta globulin fraction. Typical blood levels for chromium range from 1 to 5 mcg/liter, but blood levels are not considered a meaningful index of tissue stores. Administration of chromium supplements to chromium-deficient patients can result in normalization of the glucose tolerance curve from the diabetic-like curve typical of chromium deficiency. This response is viewed as a more meaningful indicator of chromium nutriture than serum chromium levels.

Excretion of chromium is via the kidneys, ranging from 3 to 50 mcg/day. Biliary excretion via the small intestine may be an ancillary route, but only small amounts of chromium are believed to be excreted in this manner.

INDICATIONS AND USAGE

Chromium 4 mcg/mL (Chromic Chloride Injection, USP) is indicated for use as a supplement to intravenous solutions given for TPN. Administration helps to maintain chromium serum levels and to prevent depletion of endogenous stores and subsequent deficiency symptoms.

CONTRAINDICATIONS

None known.

WARNINGS

Direct intramuscular or intravenous injection of Chromium 4 mcg/mL (Chromic Chloride Injection, USP) is contraindicated, as the acidic pH of the solution may cause considerable tissue irritation.

Severe kidney disease may make it necessary to reduce or omit chromium and zinc doses because these elements are primarily eliminated in the urine.

WARNING: This product contains aluminum that may be toxic. Aluminum may reach toxic levels with prolonged parenteral administration if kidney function is impaired. Premature neonates are particularly at risk because their kidneys are immature, and they require large amounts of calcium and phosphate solutions, which contain aluminum.

Research indicates that patients with impaired kidney function, including premature neonates, who receive parenteral levels of aluminum at greater than 4 to 5 mcg/kg/day accumulate aluminum at levels associated with central nervous system and bone toxicity. Tissue loading may occur at even lower rates of administration.

PRECAUTIONS

General

Do not use unless solution is clear and seal is intact. Chromium 4 mcg/mL (Chromic Chloride Injection, USP) should only be used in conjunction with a pharmacy directed admixture program using aseptic technique in a laminar flow environment; it should be used promptly and in a single operation without any repeated penetrations. Solution contains no preservatives; discard unused portion immediately after admixture procedure is completed.

In assessing the contribution of chromium supplements to maintenance of glucose homeostasis, consideration should be given to the possibility that the patient may be diabetic.

Geriatric Use

An evaluation of current literature revealed no clinical experience identifying differences in response between elderly and younger patients. In general, dose selection for an elderly patient should be cautious, usually starting at the low end of the dosing range, reflecting the greater frequency of decreased hepatic, renal, or cardiac function, and of concomitant disease or other drug therapy.

This drug is known to be substantially excreted by the kidney, and the risk of toxic reactions to this drug may be greater in patients with impaired renal function. Because elderly patients are more likely to have decreased renal function, care should be taken in dose selection, and it may be useful to monitor renal function.

Laboratory Tests

Because chromium is present in the bloodstream in microgram quantities, routine measurement is impractical. If necessary, samples can be sent to a reference laboratory for assay.

Carcinogenesis, Mutagenesis, and Impairment of Fertility

Long-term animal studies to evaluate the carcinogenic potential of Chromium 4 mcg/mL (Chromic Chloride Injection, USP) have not been performed, nor have studies been done to assess mutagenesis or impairment of fertility.

Nursing Mothers

It is not known whether this drug is excreted in human milk. Because many drugs are excreted in human milk, caution should be exercised when Chromium 4 mcg/mL (Chromic Chloride Injection, USP) is administered to a nursing woman.

Pediatric Use

See DOSAGE and ADMINISTRATION section. Safety and effectiveness in children have not been established.

Pregnancy

Animal reproduction studies have not been conducted with chromic chloride. It is also not known whether chromic chloride can cause fetal harm when administered to a pregnant woman or can affect reproductive capacity. Chromic chloride should be given to a pregnant woman only if clearly indicated.

ADVERSE REACTIONS

None known.

DRUG ABUSE AND DEPENDENCE

None known.

OVERDOSAGE

Trivalent chromium administered intravenously to TPN patients has been shown to be nontoxic when given at dosage levels of up to 250 mcg/day for two consecutive weeks.

Reported toxic reactions to chromium include nausea, vomiting, ulcers of the gastrointestinal tract, renal and hepatic damage, convulsions and coma. The acute LD50 for intravenous trivalent chromium in rats was reported as 10 to 18 mg/kg.

DOSAGE AND ADMINISTRATION

Chromium 4 mcg/mL (Chromic Chloride Injection, USP) contains 4 mcg chromium/mL and is administered intravenously only after dilution. The additive should be administered in a volume of fluid not less than 100 mL. For the adult receiving TPN, the suggested additive dosage is 10 to 15 mcg chromium/day (2.5 to 3.75 mL/day). The metabolically stable adult with intestinal fluid loss may require 20 mcg chromium/day (5 mL/day), with frequent monitoring of blood levels as a guideline for subsequent administration. For pediatric patients, the suggested additive dosage is 0.14 to 0.20 mcg/kg/day (0.035 to 0.05 mL/kg/day).

Parenteral drug products should be inspected visually for particulate matter and discoloration prior to administration, whenever solution and container permit. See PRECAUTIONS.

HOW SUPPLIED

Chromium (Chromic Chloride Injection, USP) is supplied as follows:

Unit of Sale | Concentration
NDC 0409-4093-10 | 40 mcg/10 mL
Tray of 25 Single-dose plastic vials | (4 mcg/mL)

Store at 20 to 25ºC (68 to 77ºF). [See USP Controlled Room Temperature.]

Distributed by Hospira, Inc., Lake Forest, IL 60045 USA

Novaplus is a registered trademark of Vizient, Inc.

LAB-1066-3.0

Revised: 4/2021

PRINCIPAL DISPLAY PANEL - 10 mL Vial Label

10 mL Single-dose Vial

CHROMIUM
Chromic Chloride Inj., USP

40 mcg/10 mL
(4 mcg/mL)

novaplus™
Distributed by Hospira, Inc.,
Lake Forest, IL 60045 USA

PRINCIPAL DISPLAY PANEL - 10 mL Vial Tray

10 mL Single-dose Vial

NDC 0409-4093-10
Contains 25 of NDC 0409-4093-09

CHROMIUM
Chromic Chloride Injection, USP

40 mcg/10 mL (4 mcg/mL)

CAUTION: FOR INTRAVENOUS
USE ONLY AFTER DILUTION.

Rx only